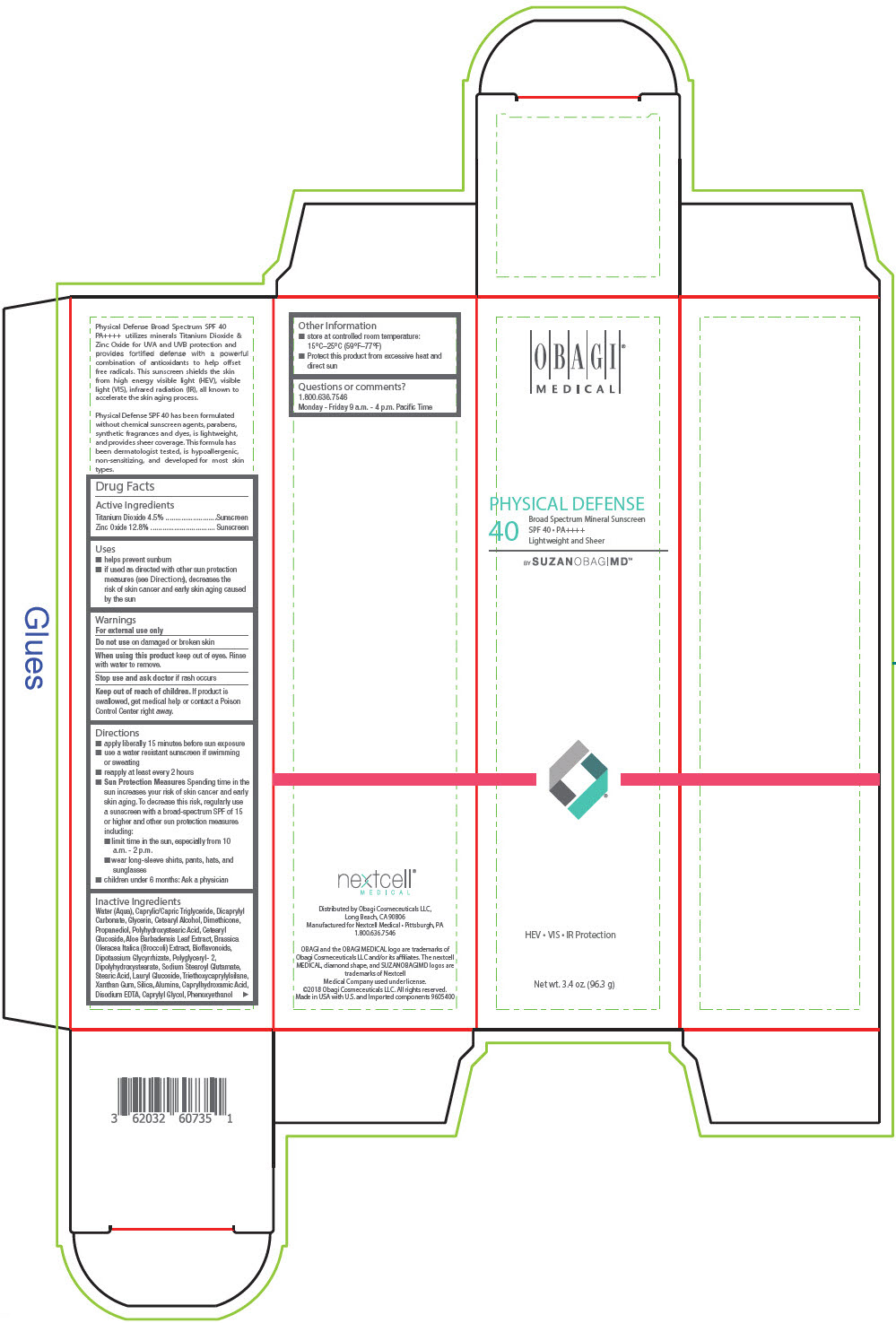 DRUG LABEL: Obagi Medical Physical Defense Broad Spectrum Mineral Sunscreen SPF 40 by SUZANOBAGIMD
NDC: 62032-607 | Form: CREAM
Manufacturer: Obagi Cosmeceuticals LLC
Category: otc | Type: HUMAN OTC DRUG LABEL
Date: 20250101

ACTIVE INGREDIENTS: TITANIUM DIOXIDE 45 mg/1 g; ZINC OXIDE 128 mg/1 g
INACTIVE INGREDIENTS: WATER; MEDIUM-CHAIN TRIGLYCERIDES; DICAPRYLYL CARBONATE; GLYCERIN; CETOSTEARYL ALCOHOL; DIMETHICONE; PROPANEDIOL; CETEARYL GLUCOSIDE; ALOE VERA LEAF; BROCCOLI; CITRUS BIOFLAVONOIDS; GLYCYRRHIZINATE DIPOTASSIUM; SODIUM STEAROYL GLUTAMATE; STEARIC ACID; LAURYL GLUCOSIDE; TRIETHOXYCAPRYLYLSILANE; XANTHAN GUM; SILICON DIOXIDE; ALUMINUM OXIDE; CAPRYLHYDROXAMIC ACID; EDETATE DISODIUM ANHYDROUS; CAPRYLYL GLYCOL; PHENOXYETHANOL

Obagi® Medical Physical Defense Broad Spectrum Mineral Sunscreen SPF 40 by SUZANOBAGIMD

Drug Facts

ACTIVE INGREDIENT

PURPOSE

Active Ingredients
Titanium Dioxide 4.5% | Sunscreen
Zinc Oxide 12.8% | Sunscreen

Uses

- helps prevent sunburn
- if used as directed with other sun protection measures (see Directions), decreases the risk of skin cancer and early skin aging caused by the sun

Warnings

For external use only

Do not use on damaged or broken skin

When using this product keep out of eyes. Rinse with water to remove.

Stop use and ask doctor if rash occurs

Keep out of reach of children. If product is swallowed, get medical help or contact a Poison Control Center right away.

Directions

- apply liberally 15 minutes before sun exposure
- use a water resistant sunscreen if swimming or sweating
- reapply at least every 2 hours
- Sun Protection Measures Spending time in the sun increases your risk of skin cancer and early skin aging. To decrease this risk, regularly use a sunscreen with a broad-spectrum SPF of 15 or higher and other sun protection measures including:
  - limit time in the sun, especially from 10 a.m. - 2 p.m.
  - wear long-sleeve shirts, pants, hats, and sunglasses
- children under 6 months: Ask a physician

Inactive Ingredients

Water (Aqua), Caprylic/Capric Triglyceride, Dicaprylyl Carbonate, Glycerin, Cetearyl Alcohol, Dimethicone, Propanediol, Polyhydroxystearic Acid, Cetearyl Glucoside, Aloe Barbadensis Leaf Extract, Brassica Oleracea Italica (Broccoli) Extract, Bioflavonoids, Dipotassium Glycyrrhizate, Polyglyceryl- 2, Dipolyhydroxystearate, Sodium Stearoyl Glutamate, Stearic Acid, Lauryl Glucoside, Triethoxycaprylylsilane, Xanthan Gum, Silica, Alumina, Caprylhydroxamic Acid, Disodium EDTA, Caprylyl Glycol, Phenoxyethanol

Other Information

- store at controlled room temperature: 15°C–25°C (59°F–77°F)
- Protect this product from excessive heat and direct sun

Questions or comments?

1.800.636.7546

Monday - Friday 9 a.m. - 4 p.m. Pacific Time

Distributed by Obagi Cosmeceuticals LLC,
Long Beach, CA 90806

PRINCIPAL DISPLAY PANEL - 96.3 g Tube Carton

OBAGI®
MEDICAL

PHYSICAL DEFENSE
40
Broad Spectrum Mineral Sunscreen
SPF 40 • PA++++
Lightweight and Sheer

BY SUZANOBAGIMD™

HEV • VIS • IR Protection

Net wt. 3.4 oz. (96.3 g)